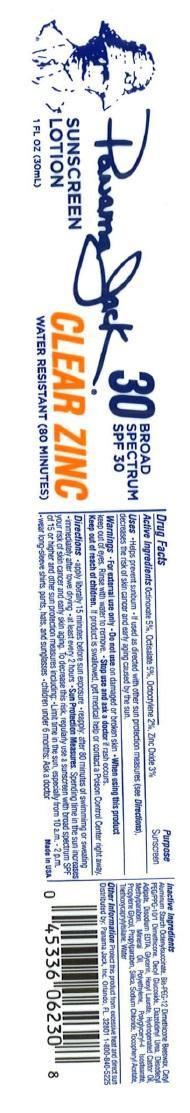 DRUG LABEL: Panama Jack
NDC: 58443-0179 | Form: LOTION
Manufacturer: Prime Enterprises, Inc.
Category: otc | Type: HUMAN OTC DRUG LABEL
Date: 20200117

ACTIVE INGREDIENTS: OCTINOXATE 49.35 mg/1 mL; OCTISALATE 49.35 1/1 mL; OCTOCRYLENE 19.74 1/1 mL; ZINC OXIDE 29.61 mg/1 mL
INACTIVE INGREDIENTS: HEXYL LAURATE; POLYGLYCERYL-4 ISOSTEARATE; DIAZOLIDINYL UREA; TRIETHOXYCAPRYLYLSILANE; METHYLPARABEN; PROPYLPARABEN; SILICON DIOXIDE; SODIUM CHLORIDE; .ALPHA.-TOCOPHEROL ACETATE; WATER; ALUMINUM STARCH OCTENYLSUCCINATE; BIS-PEG-10 DIMETHICONE/DIMER DILINOLEATE COPOLYMER; CETYL PEG/PPG-10/1 DIMETHICONE (HLB 2); DECYL GLUCOSIDE; DIISODECYL ADIPATE; GLYCERIN; HYDROGENATED CASTOR OIL; MINERAL OIL; EDETATE DISODIUM; HIGH DENSITY POLYETHYLENE

ACTIVE INGREDIENT

Active ingredients Octinoxate 5%, Octisalate 5%, Octocrylene 2%, Zinc Oxide 3%

Purpose

Sunscreen

INDICATIONS AND USAGE

Uses • Helps prevent sunburn •If used as directed with other sun protection measures (see Directions), decreases the risk of skin cancer and early skin aging caused by the sun

WARNINGS

Warnings • For external use only • Do not use on damaged or broken skin • When using this productkeep out of eyes. Rinse with water to remove. • Stop use and ask a doctorif rash occurs. • Keep out of reach of children. If product is swallowed, get medical help or contact a Poison Control Center right away.

DOSAGE AND ADMINISTRATION

Directions •apply liberally 15 minutes before sun exposure •reapply: after 80 minutes of swimming or sweating •immediately after towel drying •at least every 2 hours • Sun Protection Measures. Spending time in the sun increases your risk of skin cancer and early skin aging. To decrease this risk, regularly use a sunscreen with a broad spectrum SPF of 15 or higher and other sun protection measures including: •limit time in the sun, especially from 10 a.m. - 2 p.m. •wear long-sleeve shirts, pants, hats, and sunglasses •children under 6 months: Ask a doctor.

Inactive Ingrediets

Aluminium Starch Octenylsuccinate, Bis-PEG-12 Dimethicone Beeswax, Cetyl PEG/PPG-10/1 Dimethicone, Decyl Glucoside, Diazolidinyl Urea, Diisodecyl Adipate, Disodium EDTA, Glycerin, Hexyl Laurate, Hydrogenated Castor Oil, Methylparaben, Mineral Oil, Polyethylene, Polyglyceryl-4 Isostearate, Propylene Glycol, Propylparaben, Silica, Sodium Chloride, Tocopheryl Acetate, Triethoxycaprylysilane, Water

Other information Protect this product from excessive heat and direct sun

Distributed by: Panama Jack, Inc. Orlando, FL. 32801 1-800-840-5225

PRINCIPAL DISPLAY PANEL - 30mL Bottle Label

Panama Jack

SUNSCREEN

LOTION

1 FL OZ (30mL)

30 BROAD SPECTRUM SPF 30

CLEAR ZINC

WATER RESISTANT (80 MINUTES)